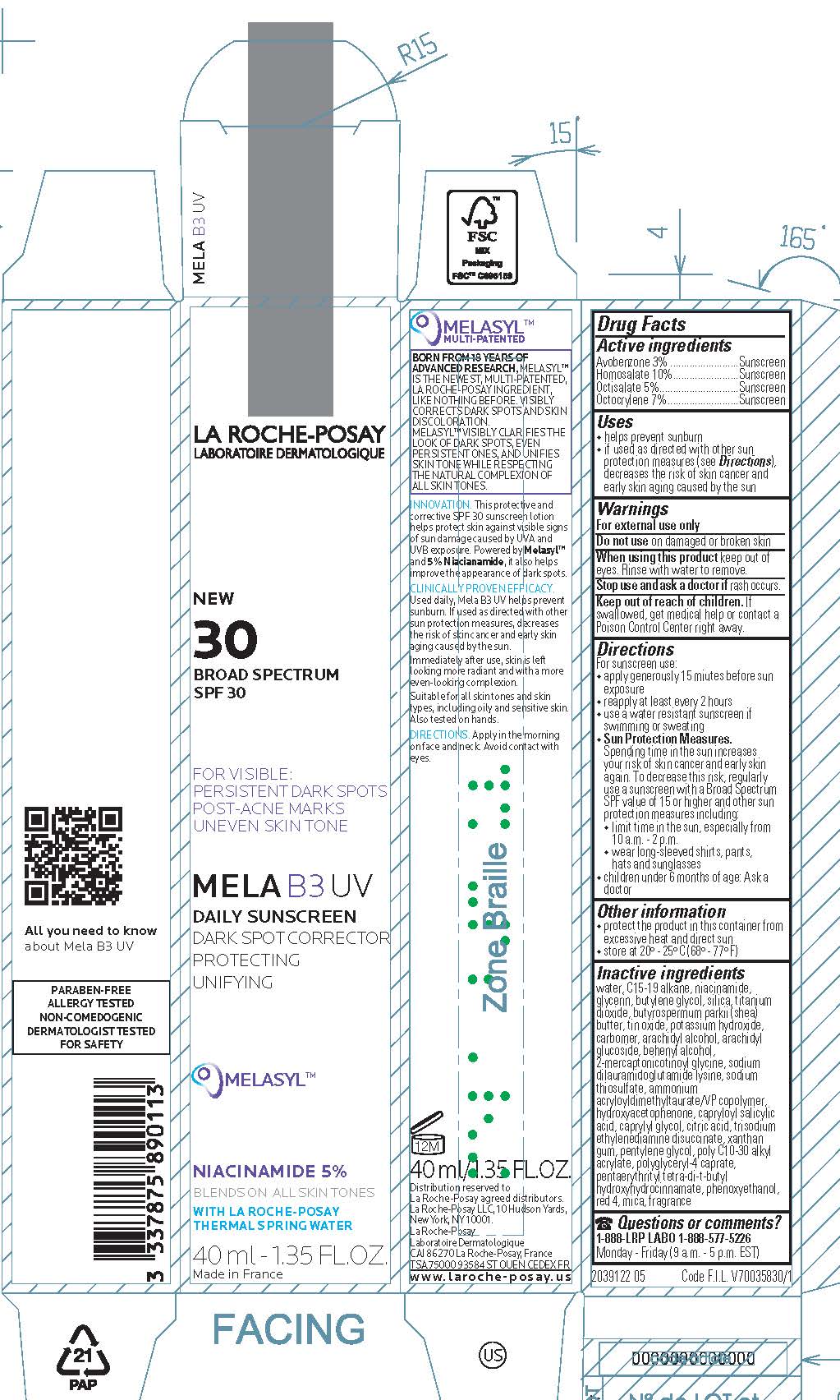 DRUG LABEL: La Roche Posay Laboratoire Dermatologique Mela B3 UV Daily Sunscreen Broad Spectrum SPF 30
NDC: 69625-113 | Form: LOTION
Manufacturer: Cosmetique Active Production
Category: otc | Type: HUMAN OTC DRUG LABEL
Date: 20231018

ACTIVE INGREDIENTS: AVOBENZONE 30 mg/1 mL; HOMOSALATE 100 mg/1 mL; OCTISALATE 50 mg/1 mL; OCTOCRYLENE 70 mg/1 mL
INACTIVE INGREDIENTS: WATER; C15-19 ALKANE; NIACINAMIDE; GLYCERIN; BUTYLENE GLYCOL; SILICON DIOXIDE; TITANIUM DIOXIDE; SHEA BUTTER; STANNIC OXIDE; POTASSIUM HYDROXIDE; CARBOMER HOMOPOLYMER, UNSPECIFIED TYPE; ARACHIDYL ALCOHOL; ARACHIDYL GLUCOSIDE; DOCOSANOL; SODIUM DILAURAMIDOGLUTAMIDE LYSINE; SODIUM THIOSULFATE; AMMONIUM ACRYLOYLDIMETHYLTAURATE/VP COPOLYMER; HYDROXYACETOPHENONE; CAPRYLOYL SALICYLIC ACID; CAPRYLYL GLYCOL; CITRIC ACID MONOHYDRATE; TRISODIUM ETHYLENEDIAMINE DISUCCINATE; XANTHAN GUM; PENTYLENE GLYCOL; BEHENYL ACRYLATE POLYMER; POLYGLYCERYL-4 CAPRATE; PENTAERYTHRITOL TETRAKIS(3-(3,5-DI-TERT-BUTYL-4-HYDROXYPHENYL)PROPIONATE); PHENOXYETHANOL; FD&C RED NO. 4; MICA

Drug Facts

Active ingredients

Avobenzone 3%
Homosalate 10%
Octisalate 5%
Octocrylene 7%

Purpose

Sunscreen

Uses

- helps prevent sunburn
- if used as directed with other sun protection measures (see Directions), decreases the risk of skin cancer and early skin aging caused by the sun

Warnings

For external use only

Do not use

on damaged or broken skin

When using this product

keep out of eyes. Rinse with water to remove.

Stop use and ask a doctor if

rash occurs

Keep out of reach of children.

If swallowed, get medical help or contact a Poison Control Center right away.

Directions

For sunscreen use:

- apply generously 15 minutes before sun exposure

- reapply at least every 2 hours

- use a water resistant sunscreen if swimming or sweating

- Sun Protection Measures. Spending time in the sun increases your risk of skin cancer and early skin aging. To decrease this risk, regularly use a sunscreen with a Broad Spectrum SPF value of 15 or higher and other sun protection measures including:

- limit time in the sun, especially from 10 a.m. - 2 p.m.

- wear long-sleeved shirts, pants, hats and sunglasses

- children under 6 months of age: Ask a doctor

Other information

- protect the product in this container from excessive heat and direct sun
- store at 20º - 25º C (68º - 77º F)

Inactive ingredients

water, c15-19 alkane, niacinamide, glycerin, butylene glycol, silica, titanium dioxide, butyrospermum parkii (shea) butter, tin oxide, potassium hydroxide, carbomer, arachidyl alcohol, arachidyl glucoside, behenyl alcohol, 2-mercaptonicotinoyl glycine, sodium dilauramidoglutamide lysine, sodium thiosulfate, ammonium acryloyldimethyltaurate/VP copolymer, hydroxyacetophenone, capryloyl salicylic acid, caprylyl glycol, citric acid, trisodium ethylenediamine disuccinate, xanthan gum, pentylene glycol, poly c10-30 alkyl acrylate, polyglyceryl-4 caprate, pentaerythrityl tetra-di-t-butyl hydroxyhydrocinnamate, phenoxyethanol, red 4, mica, fragrance

Questions or comments?

1-888-LRP LABO 1-888-577-5226

Monday - Friday (9 a.m. - 5 p.m. EST)